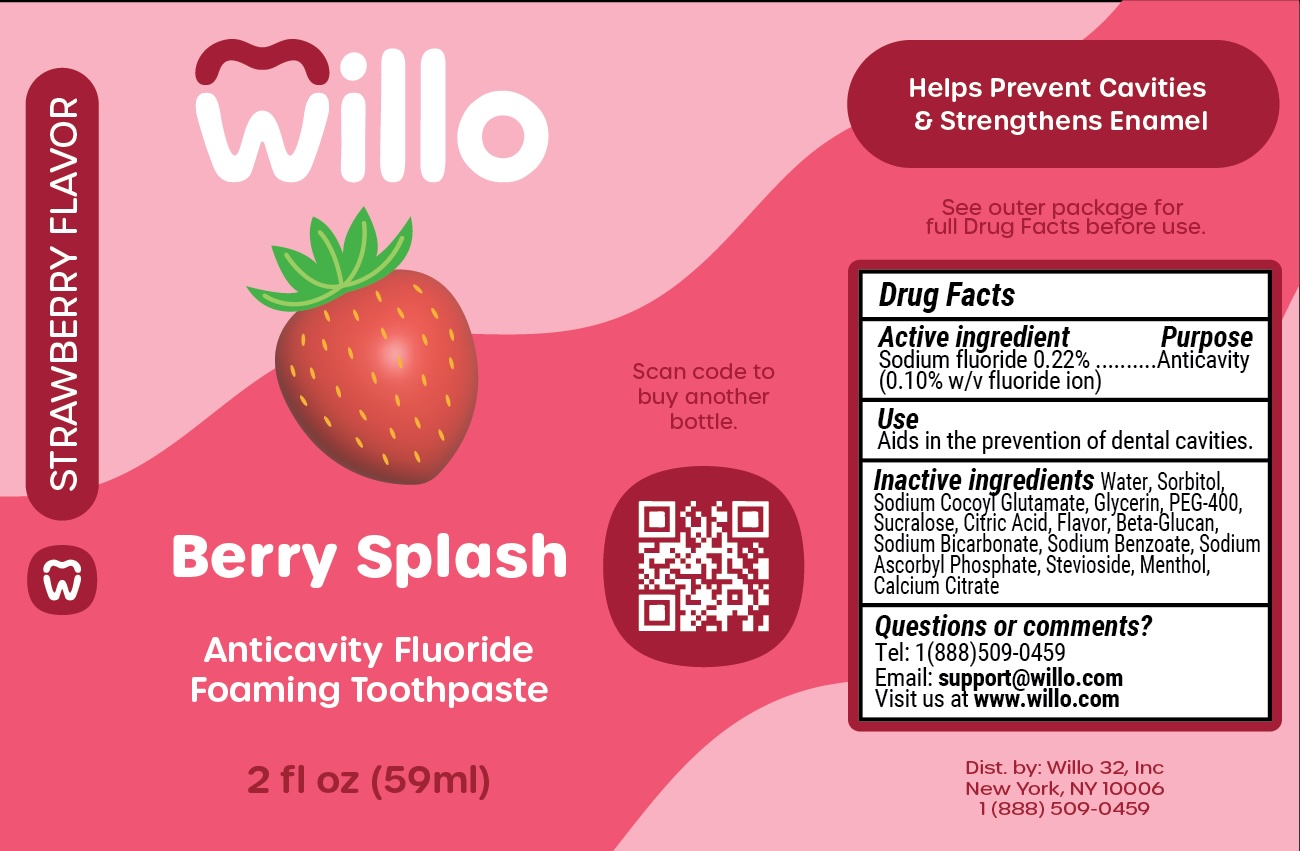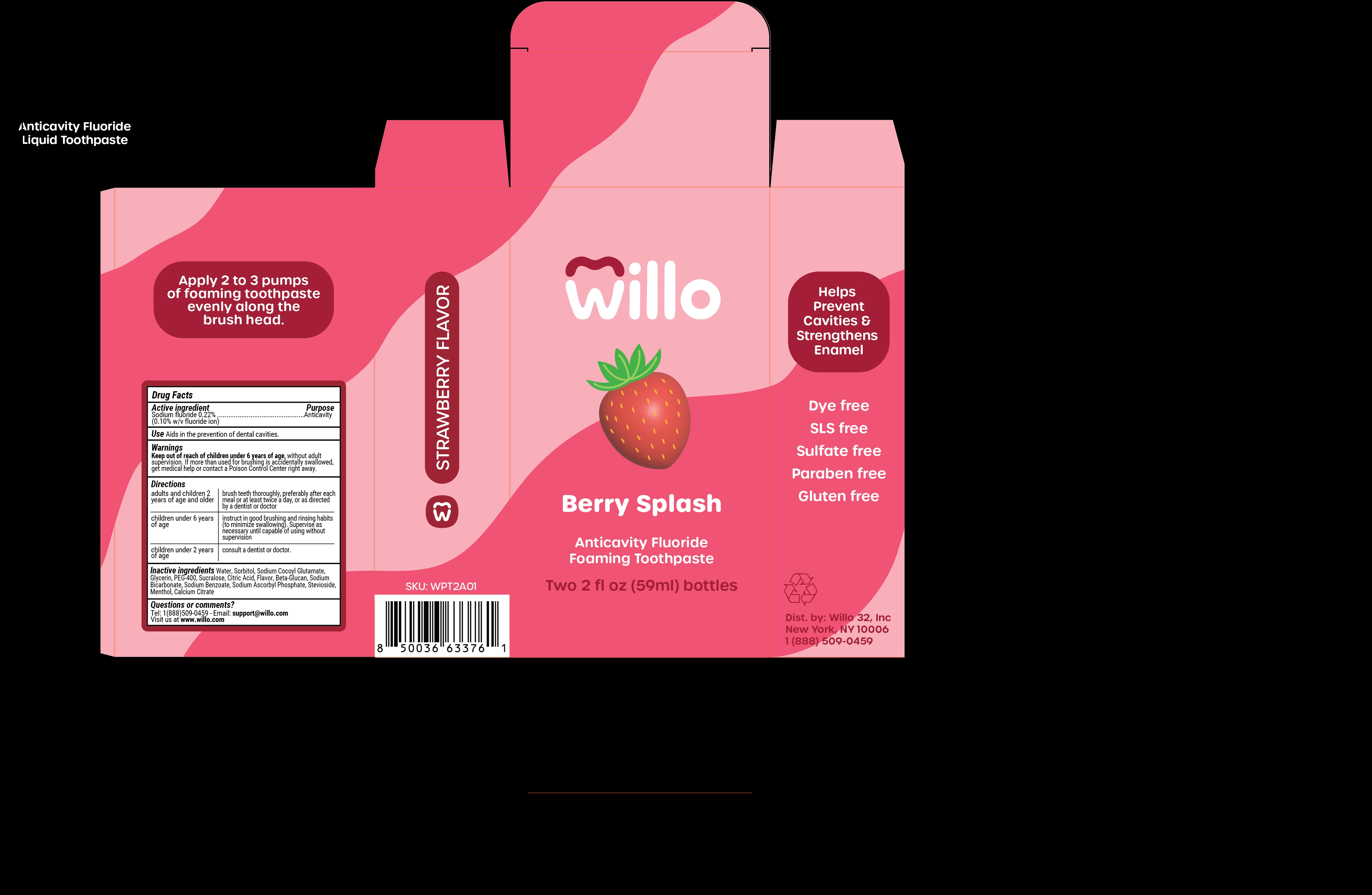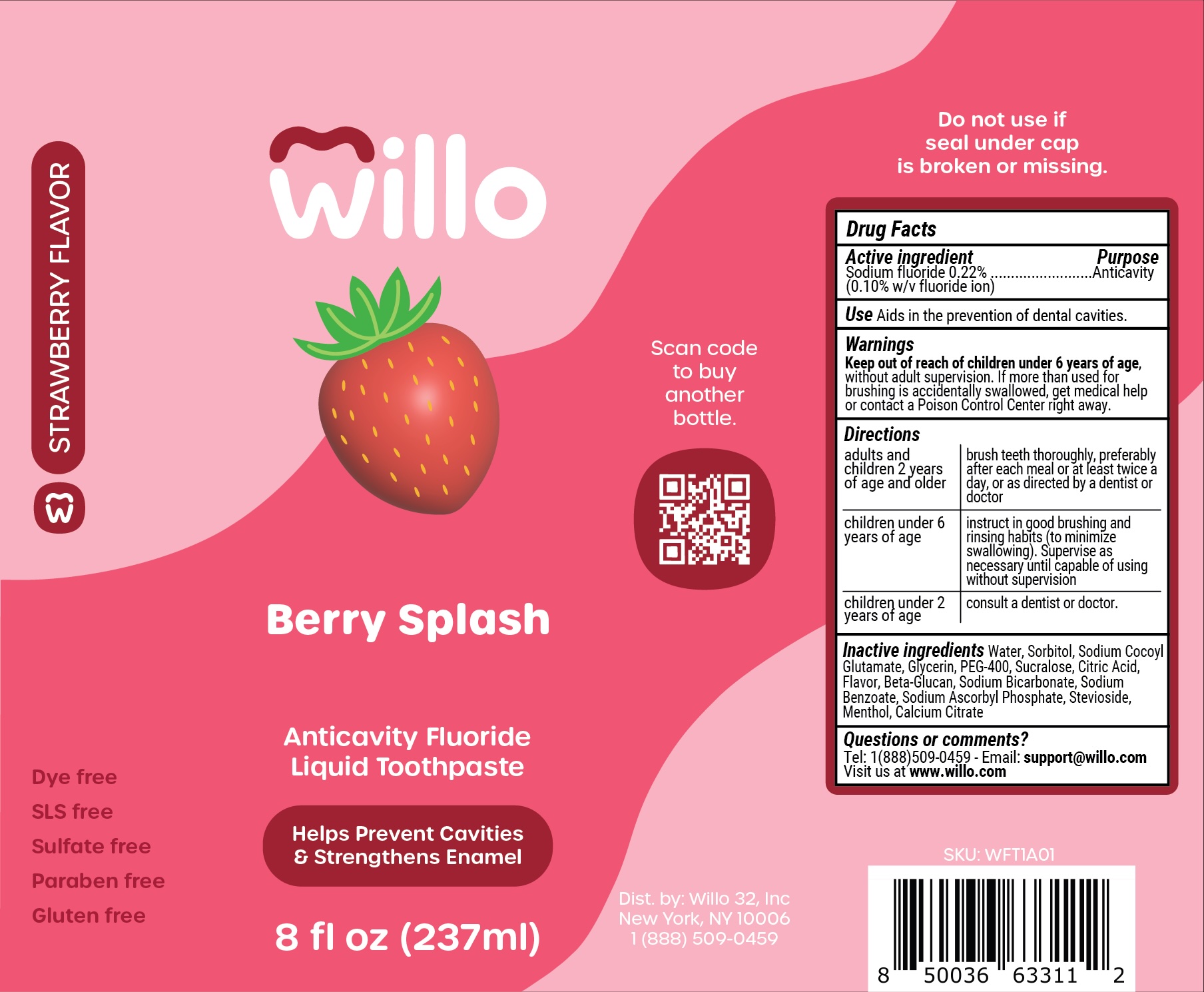 DRUG LABEL: Willo Berry Splash Dye Free
NDC: 84185-202 | Form: PASTE, DENTIFRICE
Manufacturer: Willo 32, Inc
Category: otc | Type: HUMAN OTC DRUG LABEL
Date: 20250916

ACTIVE INGREDIENTS: SODIUM FLUORIDE 1 mg/1 mL
INACTIVE INGREDIENTS: GLYCERIN; CALCIUM CITRATE; SORBITOL; PEG-400; SODIUM BICARBONATE; SODIUM ASCORBYL PHOSPHATE; MENTHOL; STEVIOSIDE; SUCRALOSE; WATER; SODIUM COCOYL GLUTAMATE; CITRIC ACID; YEAST .BETA.-D-GLUCAN; SODIUM BENZOATE

Willo Berry Splash Dye Free Fluoride Liquid Toothpaste

Application instructions

Apply 2 to 3 pumps of foaming toothpaste evenly along the brush head.

Drug Facts

Active ingredient

Sodium fluoride 0.22%

(0.10% w/v fluoride ion)

Purpose

Anticavity

Use

Use Aids in the prevention of dental cavities.

Warnings Section

Keep out of reach of children under 6 years of age, without adult supervision. If more than used for brushing is accidentally swallowed, get medical help or contact a Poison Control Center right away

Warnings

Keep out of reach of children under 6 years of age, without adult supervision. If more than used for brushing is accidentally swallowed, get medical help or contact Poison Control Center right away.

Directions

adults and children 2 years of age and older | brush teeth thoroughly, preferably after each meal or at least twice a day, or as directed by a dentist or doctor
children under 6 years of age | instruct in good brushing and rinsing habits (to minimize swallowing. Supervise as necessary until capable of using without supervision
children under 2 years of age | consult a dentist or doctor.

Inactive ingredients list

Inactive ingredients Water, Sorbitol, Sodium Cocoyl Glutamate, Glycerin, PEG-400, Sucralose, Citric Acid, Flavor, Beta-Glucan, Sodium Bicarbonate, Sodium Benzoate, Sodium Ascorbyl Phosphate, Stevioside, Menthol, Calcium Citrate

Questions section

Questions or comments?

Tel: 1(888)509-0459 - Email: support@willo.com

Visit us at www.willo.com

Flavor description

STRAWBERRY FLAVOR

Information panel

Helps Prevent Cavities & Strengthens Enamel

Dye free

SLS free

Sulfate free

Paraben free

Gluten free

♲

Dist. by: Willo 32, Inc

New York, NY 10006

1 (888) 509-0459

PACKAGE LABEL

Willo

Berry Splash

Anticavity Fluoride

Foaming Toothpaste

Two 2 fl oz (59 ml) bottles